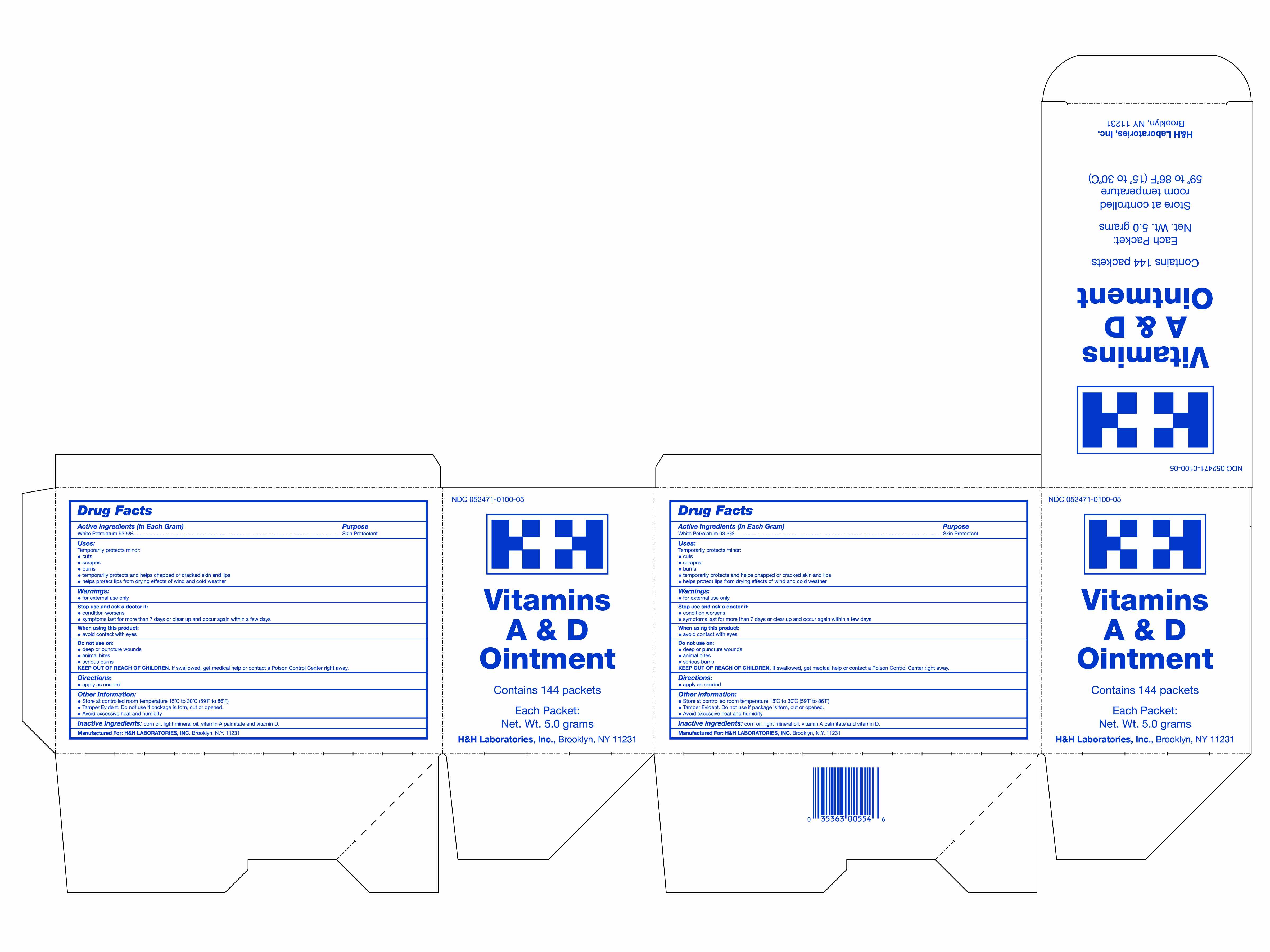 DRUG LABEL: A and D
NDC: 52471-101 | Form: OINTMENT
Manufacturer: H&H Laboratories, Inc.
Category: otc | Type: HUMAN OTC DRUG LABEL
Date: 20120514

ACTIVE INGREDIENTS: PETROLATUM 937.5 mg/1 g
INACTIVE INGREDIENTS: VITAMIN A PALMITATE; ERGOCALCIFEROL

DRUG FACTS

Active Ingredient (in each gram): White Petrolatum 93.5%

Purpose-Skin Protectant

INDICATIONS AND USAGE

Uses-Temporarily protects minor cuts, scrapes, and sunburn. Temporarily protects and helps chapped or cracked skin and lips. Helps protect lips from drying effects of wind and cold weather.

DOSAGE AND ADMINISTRATION

Directions: Apply liberally as needed Change wet and soiled diapers promptly. Cleanse the diaper area and allow to dry. Use with each diaper change, especially at bedtime when exposure to wet diapers may be prolonged.

Keep out of reach of children. If swallowed, get medical help or contact a Poison Control Center right away.

WARNINGS

For external use only. Avoid contact with eyes. on deep puncture wounds, animal bites, or serious burns.

Stop use and ask a doctor if condition worsens, symptoms last for more than 7 days or clear up and occur again within a few days.

INACTIVE INGREDIENT

Inactive Ingredients: Corn Oil, Light Mineral Oil, Vitamin A Palmitate, Vitamin D

PACKAGE LABEL

MM1